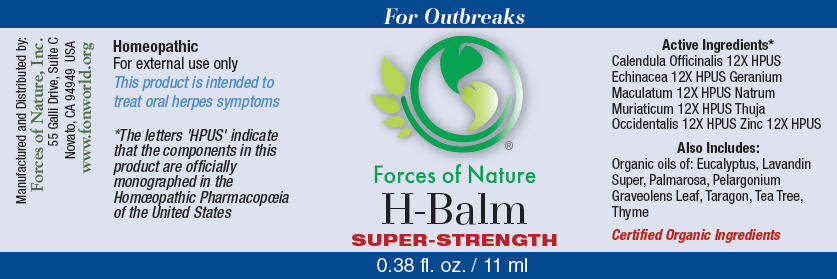 DRUG LABEL: H-Balm 
NDC: 51393-6558 | Form: SOLUTION/ DROPS
Manufacturer: Forces of Nature
Category: homeopathic | Type: HUMAN OTC DRUG LABEL
Date: 20100824

ACTIVE INGREDIENTS: CALENDULA OFFICINALIS FLOWERING TOP 12 [hp_X]/1000 mL; GERANIUM MACULATUM ROOT 12 [hp_X]/1000 mL; SODIUM CHLORIDE 12 [hp_X]/1000 mL; THUJA OCCIDENTALIS LEAFY TWIG 12 [hp_X]/1000 mL; ZINC 12 [hp_X]/1000 mL; ECHINACEA ANGUSTIFOLIA 12 [hp_X]/1000 mL

H-Balm Super Strength

Drug Facts

Indications

For the treatment of oral herpes caused by herpes simplex 1 or 2 after diagnosis by a physician. Herpes is a contagious viral infection with symptoms of rashes or blisters, redness and pain.

ACTIVE INGREDIENT

PURPOSE

Homeopathic Active Ingredients [The letters 'HPUS' indicate that the components in this product are officially monographed in the Homœopathic Pharmacopœia of the United States.]
Equal parts of: | Purpose
Calendula Officinalis 12X HPUS | Promotes healthy skin and healing
Echinacea Angustifolia 12X HPUS | Relief from skin irritation
Geranium Maculatum 12X HPUS | Relief for skin ulcers
Natrum Muriaticum 12X HPUS | Remedy for herpes, painful skin eruptions
Thuja Occidentalis 12X HPUS | Relief for herpes, skin eruptions, or burning pain
Zinc 12X HPUS | Support for immune function

Also Contains

Eucalyptus Oil, Lavandin SuperOil, Palmarosa Oil, Pelargonium Graveolens Leaf Oil, Tarragon Oil, Tea Tree Oil, Thyme Oil

Directions

Apply 2-3 drops on moistened swab and dab to problem area 3-4 times per day during an outbreak. For best results use immediately and often at the very first signs of an outbreak or when you feel one coming on. Use of this product during the prodromal phase (tingling some experience before an outbreak) may improve results. Wash hands after use. Avoid contact with eyes.

Warnings

Viral infections are contagious, and this product will not prevent the spread of the virus that causes herpes or any other virus.

WHEN USING

Some individuals may be sensitive to tea tree or other oils.

STOP USE

Begin with a small drop to determine if the product causes any increased redness or irritation and discontinue use if it irritates your skin.

PREGNANCY OR BREAST FEEDING

If you are pregnant or breast-feeding, ask a health professional before use.

Keep out of the reach of children.

If accidental ingestion of more than several drops, get medical help or contact a Poison Control Center.

WHEN USING

For external use only. Avoid contact with eyes.

Stop use and ask a doctor if condition worsens or symptoms last more than 7 days.

Manufactured by:
Forces of Nature, Inc.
55 Galli Drive, Suite C
Novato, CA 94949 USA
www.fonworld.org

Product questions?

877-975-3797

NDC #: 1393-6558-1 (11ml) //51393-6558-2 (33ml)

PRINCIPAL DISPLAY PANEL - 11 ml Bottle Label

For Outbreaks

Forces of Nature

H-Balm

SUPER-STRENGTH

0.38 fl. oz. / 11 ml